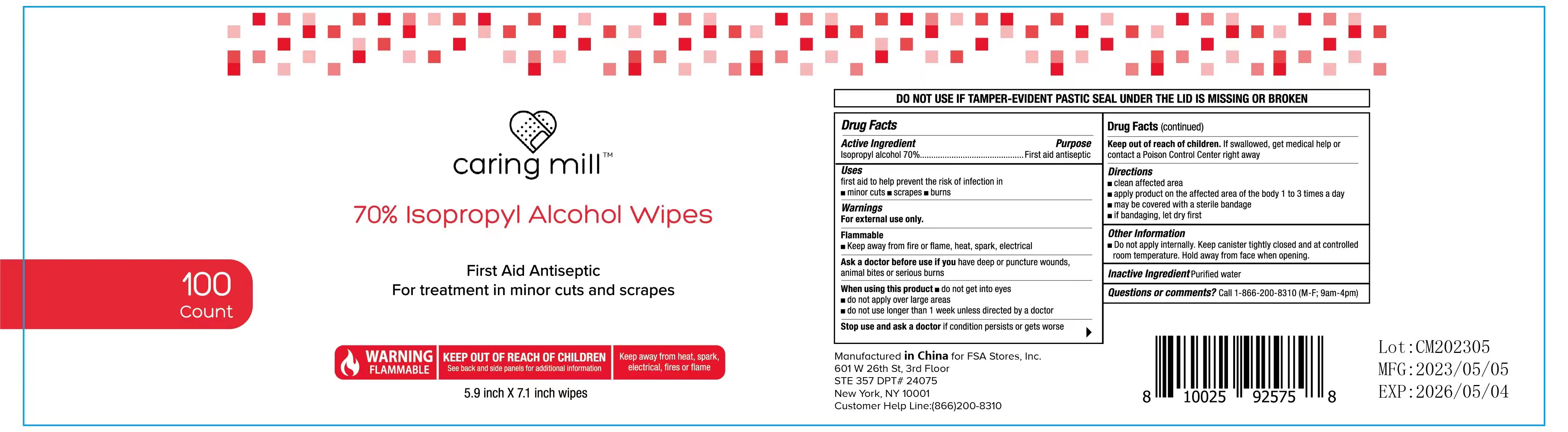 DRUG LABEL: 70% Isopropyl Alcohol Wipes
NDC: 78536-009 | Form: CLOTH
Manufacturer: Zhejiang Yiwu Mingou Biotechnology Co., Ltd.
Category: otc | Type: HUMAN OTC DRUG LABEL
Date: 20230819

ACTIVE INGREDIENTS: ISOPROPYL ALCOHOL 70 mL/100 mL
INACTIVE INGREDIENTS: WATER

78536-009 70% Isopropyl Alcohol Wipes

ACTIVE INGREDIENT

Isopropyl Alcohol 70%

PURPOSE

First aid antiseptic

USE

first aid to help prevent the risk of infection in

minor cuts scrapes burns

Warning

For external use only.

Flammable
Keep away from fire or flame, heat, spark, electrical
Ask a doctor before use if you have deep or puncture wounds,animal bites or serious burns
when using this product m do not get into eyes

do not apply over large areas
do not use longer than 1 week unless directed by a doctor

Stop use and ask a doctor if condition persists or gets worse

Keep out of reach of children. If swallowed, get medical help orcontact a Poison Control Center right away

Directions

clean affected area
apply product on the affected area of the body 1 to 3 times a day

may be covered with a sterile bandage
if bandaging, let dry first
Other Information
Do not apply internally. Keep canister tightly closed and at controlledroom temperature.Hold away from face when opening.

Inactive ingredients

Purified water